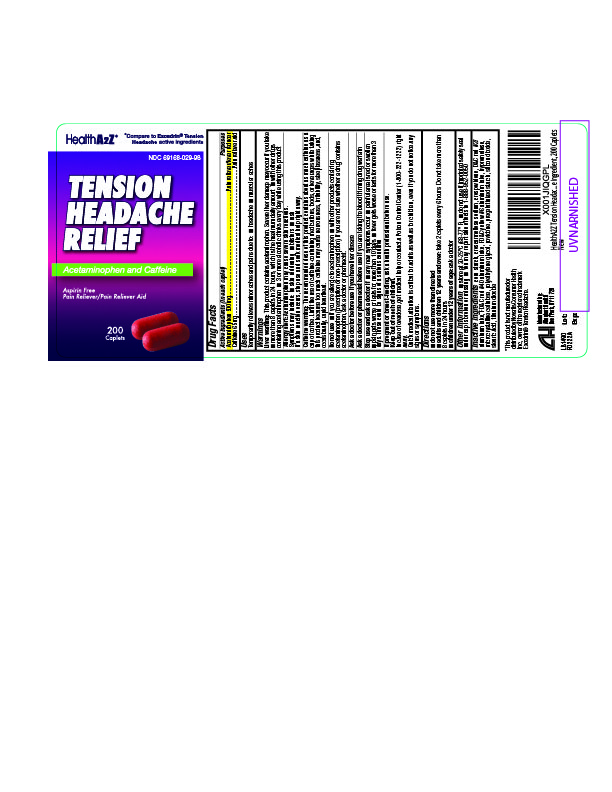 DRUG LABEL: Tension Headache Relief
NDC: 69168-029 | Form: CAPSULE
Manufacturer: Allegiant Health
Category: otc | Type: HUMAN OTC DRUG LABEL
Date: 20171116

ACTIVE INGREDIENTS: ACETAMINOPHEN 500 mg/1 1; CAFFEINE 65 mg/1 1
INACTIVE INGREDIENTS: SILICON DIOXIDE; STARCH, CORN; CROSCARMELLOSE SODIUM; D&C RED NO. 27; FD&C RED NO. 40; FD&C YELLOW NO. 6; HYPROMELLOSES; CELLULOSE, MICROCRYSTALLINE; POLYETHYLENE GLYCOL, UNSPECIFIED; STEARIC ACID; TITANIUM DIOXIDE

Drug Facts

Active ingredient (in each caplet)

Acetaminophen 500 mg
Caffeine 65mg

Purpose

Pain reliever
Pain reliever aid

Uses

temporary relief of minor aches and pains due to ■ headache ■ muscular aches

Warnings

Liver warning: This product contains acetaminophen. Severe liver damage may occur if you ■ take more than 8 tablets in 24 hours, which is the maximum daily amount

■ take with other drugs containing acetaminophen ■ have 3 or more alcoholic drinks every day while using this product

Allergy alert: Aspirin may cause a severe allergic reaction which may include: ■ hives ■ facial swelling

■ asthma (wheezing) ■ shock

Acetaminophen may cause severe skin reactions. Symptoms may include: ■ skin reddening ■ blisters ■ rash
If a skin reaction occurs, stop use and seek medical help right away.

Caffeine warning: The recommended dose of this product contains about as much caffeine as a cup of coffee. Limit the use of caffeine-containing medications, foods, or beverages while taking this product because too much caffeine may cause nervousness, irritability, sleeplessness, and occasionally rapid heartbeat.

Do Not Use

■ with any other drug containing acetaminophen (prescription or nonprescription). Ask a doctor or pharmacist before using with other drugs if you are not sure.

Ask doctor before use if you have

liver disease

Stop Use and ask a doctor if

■ any new symptoms occur ■ symptoms do not get better or worsen ■ painful area is red or swollen ■ pain gets worse or lasts for more than 10 days ■ fever gets worse or lasts for more than 3 days

If pregnant or breast-feeding,

ask a health professional before use.

Keep out of reach of children.

In case of accidental overdose, get medical help or contact a PoisonControlCenter immediately. Prompt medical attention is critical for adults as well as for children even if you do not notice any signs or symptoms

Directions

Do not exceed recommended dosage.
Adults and children 12 years and over: take 2 tablets every 6 hours. Do not take more than 8 tablets in 24 hours
Children under 12 years: ask a doctor

Inactive Ingredients

corn starch, croscarmellose sodium, crospovidone, D&C red #27 aluminum lake, FD&C red #40 aluminum lake, FD&C yellow #6 aluminum lake, hypromellose, microcrystalline cellulose, polyethylene glycol, povidone, pregelatinized starch, silicon dioxide, stearic acid, titanium dioxide

Package/Label Principal Display Panel

Tension Headache
Health A2Z®

*Compare to the active ingredients in Excedrin® Tension Headache

See new warnings information

TENSION HEADACHE RELIEF
Acetaminophen and Caffeine
Aspirin Free
Pain Reliever/Pain Reliever Aid

Caplets